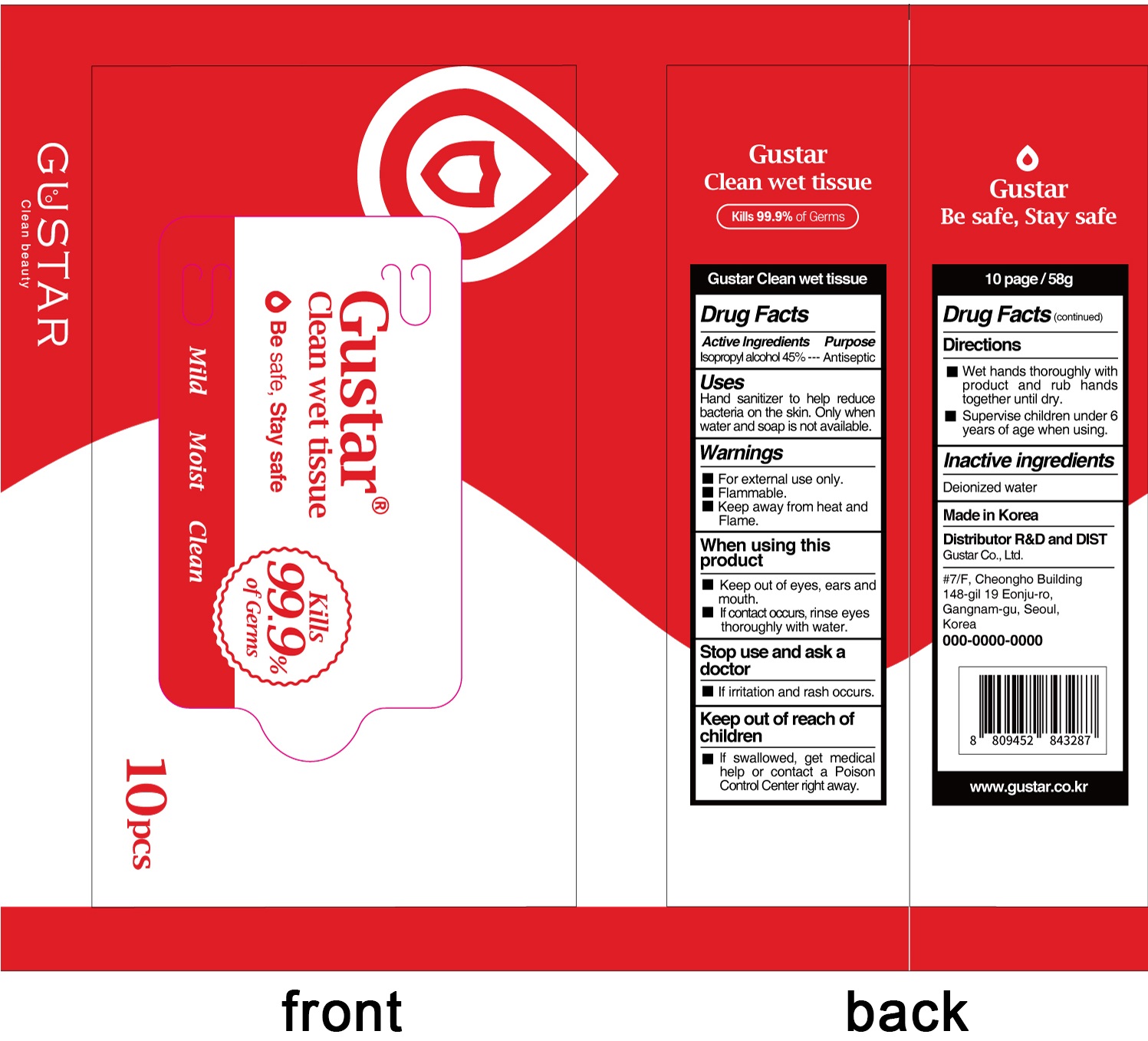 DRUG LABEL: Gustar Clean wet tissue
NDC: 73819-0008 | Form: CLOTH
Manufacturer: GuStar Co., Ltd.
Category: otc | Type: HUMAN OTC DRUG LABEL
Date: 20201218

ACTIVE INGREDIENTS: ISOPROPYL ALCOHOL 0.45 1/1 1
INACTIVE INGREDIENTS: Water

ACTIVE INGREDIENT

Isopropyl Alcohol 45%

INACTIVE INGREDIENT

Deionized water

PURPOSE

Antiseptic

WARNINGS

■ For external use only.
■ Flammable. ■ Keep away from heat and Flame.

------------------------------------------------------------------

When using this product
■ Keep out of eyes, ears and mouth.
■ If contact occurs, rinse eyes thoroughly with water.

------------------------------------------------------------------
Stop use and ask a doctor
■ If irritation and rash occurs.

KEEP OUT OF REACH OF CHILDREN

■ lf swallowed, get medical help or contact a Poison Control Center right away.

Uses

Hand sanitizer to help reduce bacteria on the skin. Only when water and soap is not available.

Directions

■ Wet hands thoroughly with product and rub hands together until dry.
■ Supervise children under 6 years of age when using.